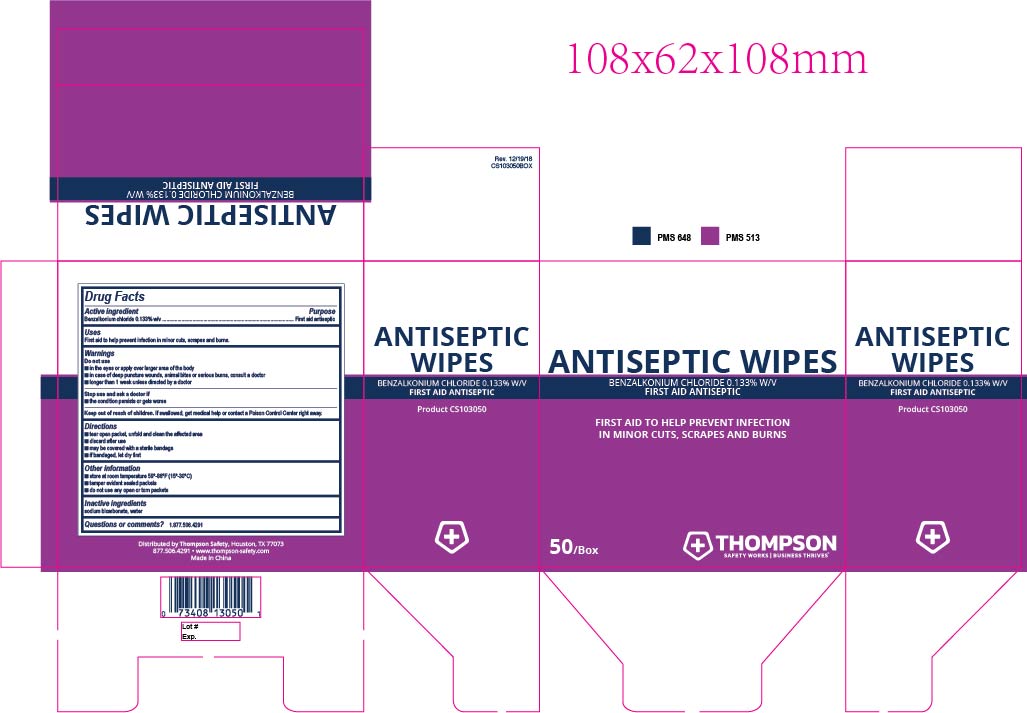 DRUG LABEL: Thompson Antiseptic
NDC: 73408-034 | Form: SWAB
Manufacturer: Thompson
Category: otc | Type: HUMAN OTC DRUG LABEL
Date: 20240904

ACTIVE INGREDIENTS: BENZALKONIUM CHLORIDE 1.3 mg/1 mL
INACTIVE INGREDIENTS: WATER; SODIUM BICARBONATE

Thompson Antiseptic

ACTIVE INGREDIENT

Benzalkonium chloride 0.133% w/v

PURPOSE

First aid antiseptic

INDICATIONS AND USAGE

First aid to help prevent infection in minor cuts, scrapes and burns.

WARNINGS

in the eyes or over large areas of the body
in case of deep or puncture wounds, animal bites or serious burns, consult a doctor
longer than 1 week unless directed by a doctor

DO NOT USE

in the eyes or over large areas of the body
in case of deep or puncture wounds, animal bites or serious burns, consult a doctor
longer than 1 week unless directed by a doctor

STOP USE

the condition persists or gets worse

KEEP OUT OF REACH OF CHILDREN

If swallowed, get medical help or contact a Poison Control Center right away.

DOSAGE AND ADMINISTRATION

tear open packet, unfold and celan the affected area
discard after use
may be covered with a sterile bandage
if bandaged, let dry first

OTHER SAFETY INFORMATION

store at room temperature 59-86°F (15-30°C)

tamper evident sealed packets

do not use any open or torn packets

INACTIVE INGREDIENT

sodium bicarbonate, water

QUESTIONS

1.877.506.4291

PACKAGE LABEL

Antiseptic Wipes

Benzalonium Chloride 0.133% W/V

FIRST AID ANTISEPTIC

FIRST AID TO HELP PREVENT INFECTION IN MINOR CUTS, SCRAPES AND BURNS

50/Box

THOMPSON
SAFETY WORKS BUSINESS THRIVES ᵀᴹ